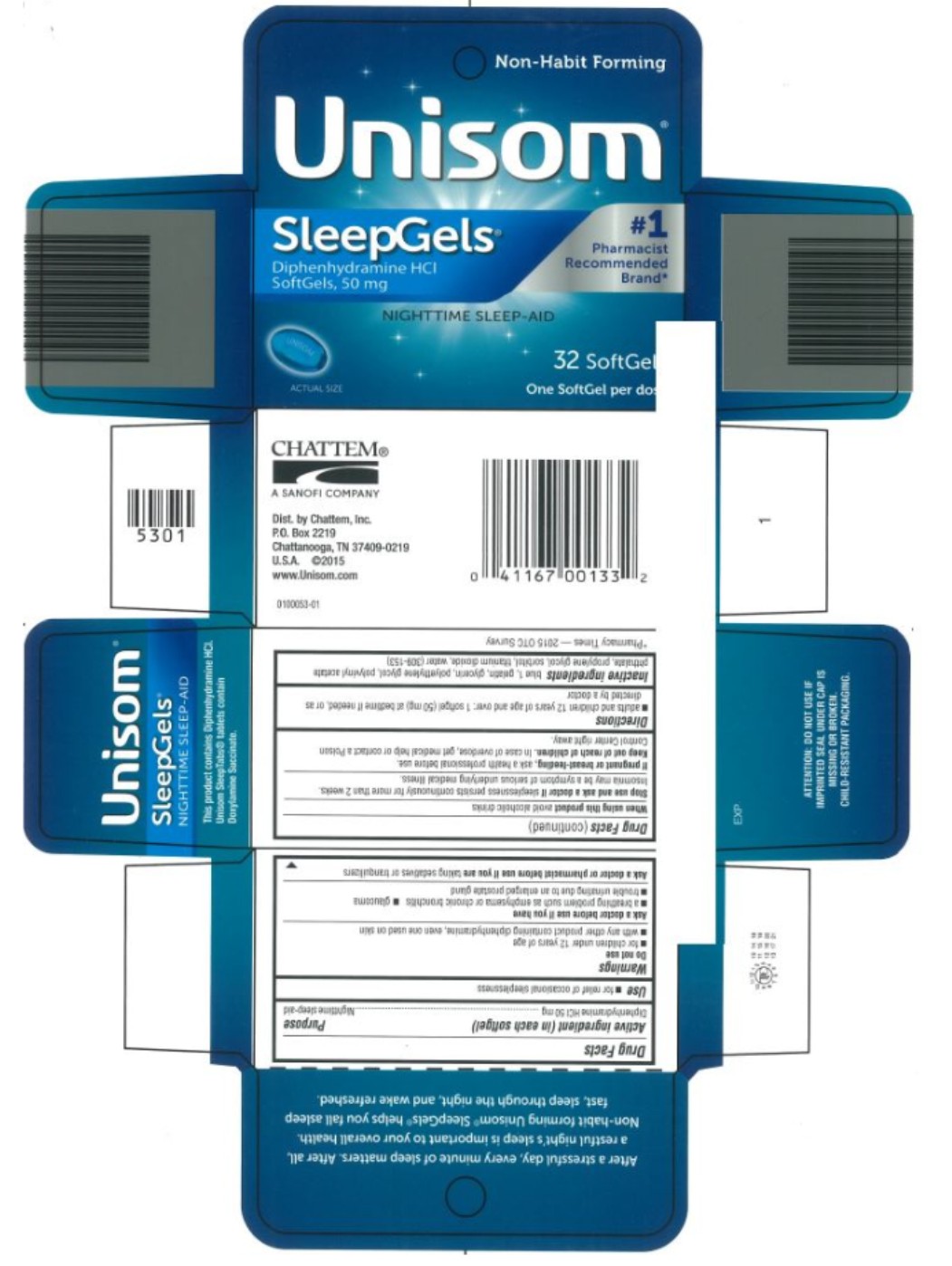 DRUG LABEL: Unisom SleepGels Nighttime Sleep-Aid
NDC: 41167-0061 | Form: CAPSULE, LIQUID FILLED
Manufacturer: Chattem, Inc.
Category: otc | Type: HUMAN OTC DRUG LABEL
Date: 20260114

ACTIVE INGREDIENTS: DIPHENHYDRAMINE HYDROCHLORIDE 50 mg/1 1
INACTIVE INGREDIENTS: FD&C BLUE NO. 1; GELATIN; GLYCERIN; POLYETHYLENE GLYCOL, UNSPECIFIED; Polyvinyl Acetate Phthalate; PROPYLENE GLYCOL; SORBITOL; TITANIUM DIOXIDE; WATER

Unisom SleepGels Nighttime

Drug Facts

Active ingredient

(in each softgel)

Diphenhydramine HCI 50 mg

Purpose

Nighttime sleep-aid

Use

- for relief of occasional sleeplessness

Warnings

Do not use

- for children under 12 years of age
- with any other product containing diphenhydramine, even one used on skin

Ask a doctor before use if you have

- a breathing problem such as emphysema or chronic bronchitis
- glaucoma
- trouble urinating due to an enlarged prostate gland

Ask a doctor or pharmacist before use if you are

taking sedatives or tranquilizers

When using this product

avoid alcoholic drinks

Stop use and ask a doctor if

sleeplessness persist continuously for more than 2 weeks. Insomnia may be a symptom of serious underlying medical illness.

If pregnant or breast-feeding,

ask a health professional before use.

Keep out of reach of children.

In case of overdose, get medical help or contact a Poison Control Center right away.

Directions

- adults and children 12 years of age and over: 1 softgel (50 mg) at bedtime if needed, or as directed by a doctor

Inactive ingredients

blue 1, gelatin, glycerin, polyethylene glycol, polyvinyl acetate phthalate, propylene glycol, sorbitol, titanium dioxide, water (309-153)

PRINCIPAL DISPLAY PANEL

Unisom
SleepGels
Diphenhydramine HCI
SoftGels, 50 mg
#1 Pharmacist Recommended Brand*
NIGHTTIME SLEEP-AID
32 SoftGels
One SoftGel per dose